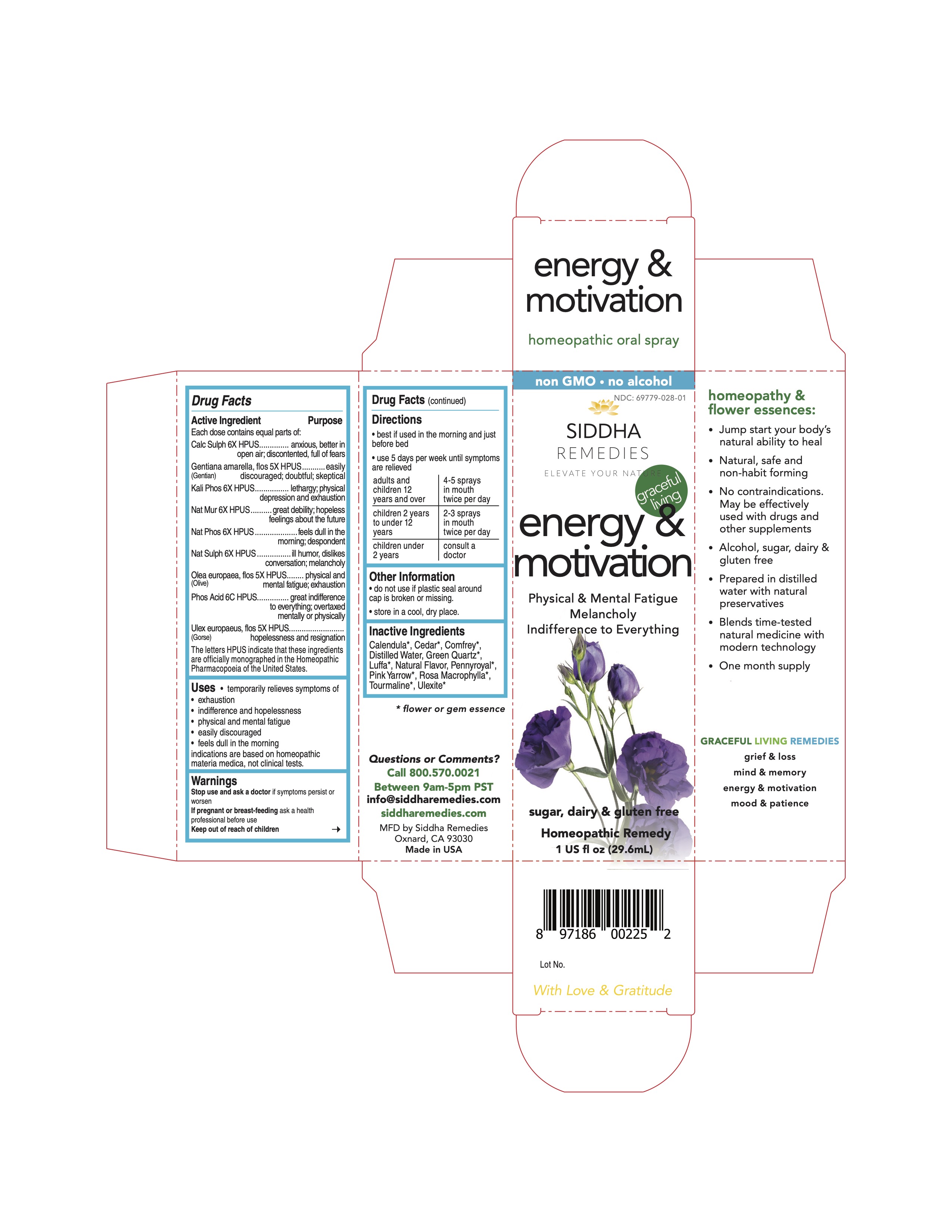 DRUG LABEL: energy and motivation
NDC: 69779-028 | Form: SPRAY
Manufacturer: Siddha Flower Essences LLC
Category: homeopathic | Type: HUMAN OTC DRUG LABEL
Date: 20251231

ACTIVE INGREDIENTS: CALCIUM SULFATE ANHYDROUS 6 [hp_X]/29.6 mL; GENTIANELLA AMARELLA FLOWER 5 [hp_X]/29.6 mL; DIBASIC POTASSIUM PHOSPHATE 6 [hp_X]/29.6 mL; SODIUM CHLORIDE 6 [hp_X]/29.6 mL; SODIUM PHOSPHATE, DIBASIC, HEPTAHYDRATE 6 [hp_X]/29.6 mL; SODIUM SULFATE 6 [hp_X]/29.6 mL; OLEA EUROPAEA FLOWER 5 [hp_X]/29.6 mL; PHOSPHORIC ACID 6 [hp_C]/29.6 mL; ULEX EUROPAEUS FLOWER 5 [hp_X]/29.6 mL
INACTIVE INGREDIENTS: CALENDULA OFFICINALIS FLOWERING TOP; CEDAR LEAF OIL; COMFREY; LUFFA; PENNYROYAL OIL; ACHILLEA MILLEFOLIUM FLOWERING TOP; WATER

Active Ingredient

Each dose contains equal parts of:

Calc Sulph 6X HPUS

Gentiana amarella, flos (Gentian) 5X HPUS

Kali Phos 6X HPUS

Nat Mur 6X HPUS

Nat Phos 6X HPUS

Nat Sulph 6X HPUS

Olea europea, flos (Olive) 5X HPUS

Phos Acid 6C HPUS

Ulex europaeus, flos (Gorse) 5X HPUS

Purpose

Each dose contains equal parts of:

Calc Sulph 6X HPUS......................................anxious, better in open air; discontented, full of fears

Gentiana amarella, flos (Gentian) 5X HPUS......easily discouraged; doubtful; skeptical

Kali Phos 6X HPUS........................................lethargy; physical depression and exhaustion

Nat Mur 6X HPUS.........................................great debility; hopeless feelings about the future

Nat Phos 6X HPUS.......................................feels dull in the morning; despondent

Nat Sulph 6X HPUS......................................ill humor, dislikes conversation; melancholy

Olea europea, flos (Olive) 5X HPUS................physical and mental fatigue; exhaustion

Phos Acid 6C HPUS......................................great indifference to everything; overtaxed mentally or physically

Ulex europaeus, flos (Gorse) 5X HPUS...........hopelessness and resignation

Uses

temporarily relieves symptoms of

- exhaustion
- indifference and hopelessness
- physical and mental fatigue
- easily discouraged
- feels dull in the morning

indications are based on homeopathic materia medica, not clinical tests.

Uses

Stop use and ask a doctor if symptoms persist or worsen

PREGNANCY OR BREAST FEEDING

If pregnant or breast-feeding ask a health professional before use

Keep out of reach of children

Directions

- best if used in the morning and just before bed
- use 5 days per week until symptoms are relieved

adults and children 12 years and over | 4-5 sprays in mouth twice per day
children 2 years to under 12 years | 2-3 sprays in mouth twice per day
children under 2 years | consult a doctor

Other Information

- do not use if plastic seal around cap is broken or missing.
- store in a cool, dry place.

Inactive Ingredients

Calendula*, Cedar*, Comfrey*, Green Quartz*, Luffa*, Natural Flavor, Pennyroyal*, Pink Yarrow*, Purified Water, Rosa Macrophylla*, Tourmaline*, Ulexite*

*flower or gem essence

Questions or Comments?
Call 800.570.0021
Between 9am-5pm PST
info@siddhaflowers.com
siddhaflowers.com
MFD by Siddha Flower Essences
Oxnard, CA 93030
Made in USA

Side Panel

homeopathy and flower essences:

- Jump start your body's natural ability to heal
- Natural, safe and non-habit forming
- No contraindications. May be effectively used with drugs and other supplements
- Alcohol, sugar, dairy and gluten free
- Prepared in purified water with natural preservatives
- Blends time-tested natural medicine with modern technology
- One month supply

GRACEFUL AGING REMEDIES

grief & loss

mind & memory

energy & motivation

mood & patience

Principal Display Panel

non GMO - no alcohol
siddha cell salts + flower essences
energy & motivation

Physical & Mental fatigue

Melancholy

Indifference to Everything

sugar, dairy & gluten free
Homeopathic Remedy
1 US fl oz (29.6mL)